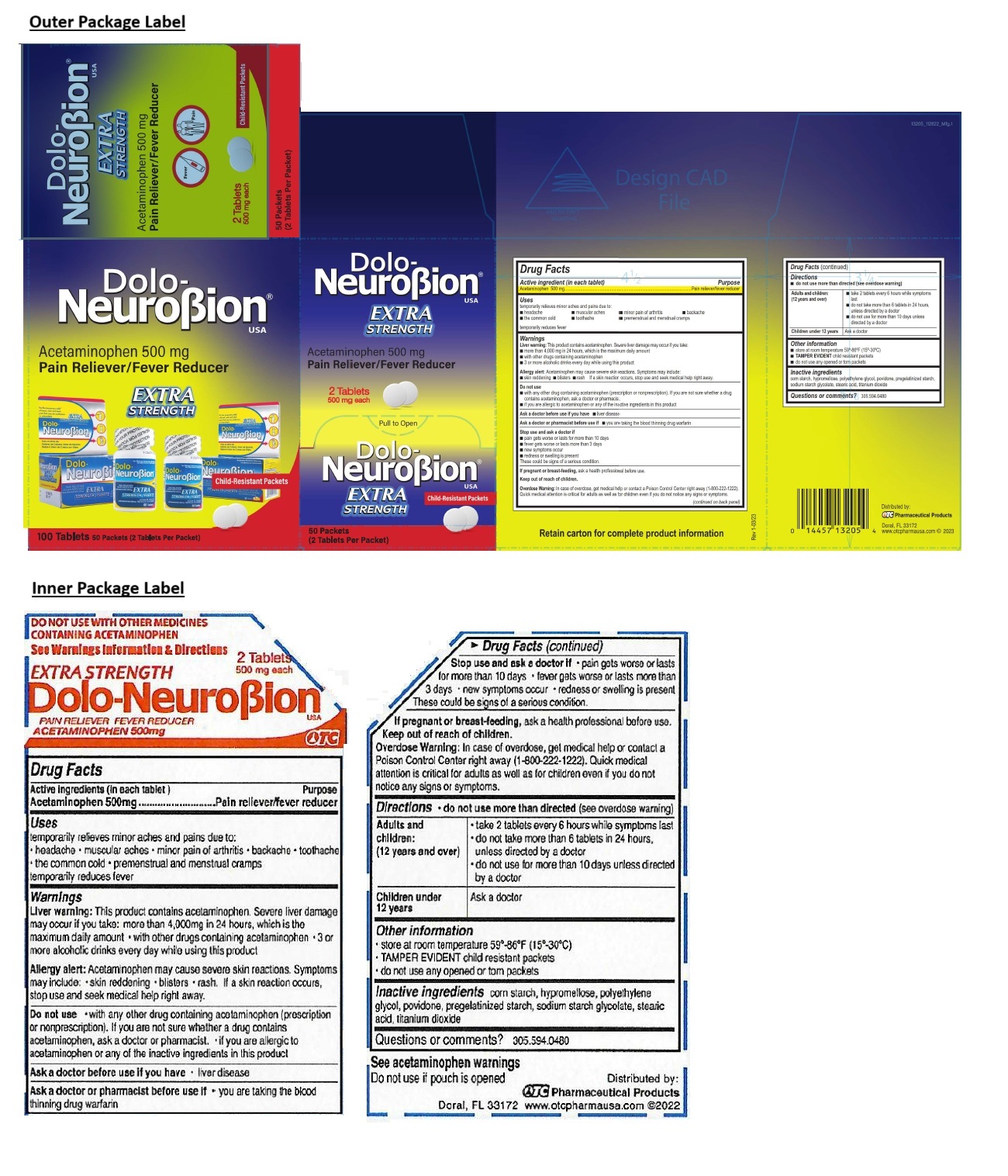 DRUG LABEL: Dolo-NeuroBion
NDC: 55959-131 | Form: TABLET, FILM COATED
Manufacturer: BENARD INDUSTRIES INC
Category: otc | Type: HUMAN OTC DRUG LABEL
Date: 20250604

ACTIVE INGREDIENTS: ACETAMINOPHEN 500 mg/1 1
INACTIVE INGREDIENTS: STARCH, CORN; HYPROMELLOSE, UNSPECIFIED; POLYETHYLENE GLYCOL, UNSPECIFIED; POVIDONE, UNSPECIFIED; SODIUM STARCH GLYCOLATE TYPE A POTATO; STEARIC ACID; TITANIUM DIOXIDE

EXTRA STRENGTH Dolo-NeuroBion® USA

Active ingredient (in each tablet)

Acetaminophen 500 mg

Purpose

Pain reliever/fever reducer

Uses

temporarily relieves minor aches and pains due to:
• headache • muscular aches • minor pain of arthritis • backache • the common cold • toothache • premenstrual and menstrual cramps

temporarily reduces fever

Warnings

Liver warning: This product contains acetaminophen. Severe liver damage may occur if you take:
• more than 4,000 mg in 24 hours, which is the maximum daily amount
• with other drugs containing acetaminophen
• 3 or more alcoholic drinks every day while using this product

Allergy alert: Acetaminophen may cause severe skin reactions. Symptoms may include: • skin reddening • blisters • rash
If a skin reaction occurs, stop use and seek medical help right away.

Do not use
• with any other drug containing acetaminophen (prescription or nonprescription). If you are not sure whether a drug contains acetaminophen, ask a doctor or pharmacist.
• if you are allergic to acetaminophen or any of the inactive ingredients in this product

Ask a doctor before use if you have • liver disease

Ask a doctor or pharmacist before use if • you are taking the blood thinning drug warfarin

Stop use and ask a doctor if
• pain gets worse or lasts more than 10 days
• fever gets worse or lasts more than 3 days
• new symptoms occur
• redness or swelling is present

These could be signs of a serious condition.

If pregnant or breast-feeding, ask a health professional before use.

Keep out of reach of children.

Overdose Warning: In case of overdose, get medical help or contact a Poison Control Center right away (1-800-222-1222).
Quick medical attention is critical for adults as well as for children even if you do not notice any signs or symptoms.

Directions

• do not use more than directed (see overdose warning)

Adults and children: (12 years and over) | • take 2 tablets every 6 hours while symptoms last; • do not take more than 6 tablets in 24 hours, unless directed by a doctor; • do not use for more than 10 days unless directed by a doctor
Children under 12 years | Ask a doctor

Other information

• store at room temperature 59°-86°F (15°-30°C)
• TAMPER EVIDENT child resistant packets
• do not use any opened or torn packets

Inactive ingredients

corn starch, hypromellose, polyethylene glycol, povidone, pregelatinized starch, sodium starch glycolate, stearic acid, titanium dioxide

Questions or comments?

305.594.0480

EXTRA STRENGTH

DO NOT USE WITH OTHER MEDICINES
CONTAINING ACETAMINOPHEN

See Warnings Information & Directions

See acetaminophen warnings
Do not use if pouch is opened

Child-Resistant Packets

Retain carton for complete product information

Distributed by:
OTC Pharmaceutical Products
Doral, FL 33172
www.otcpharmausa.com © 2023